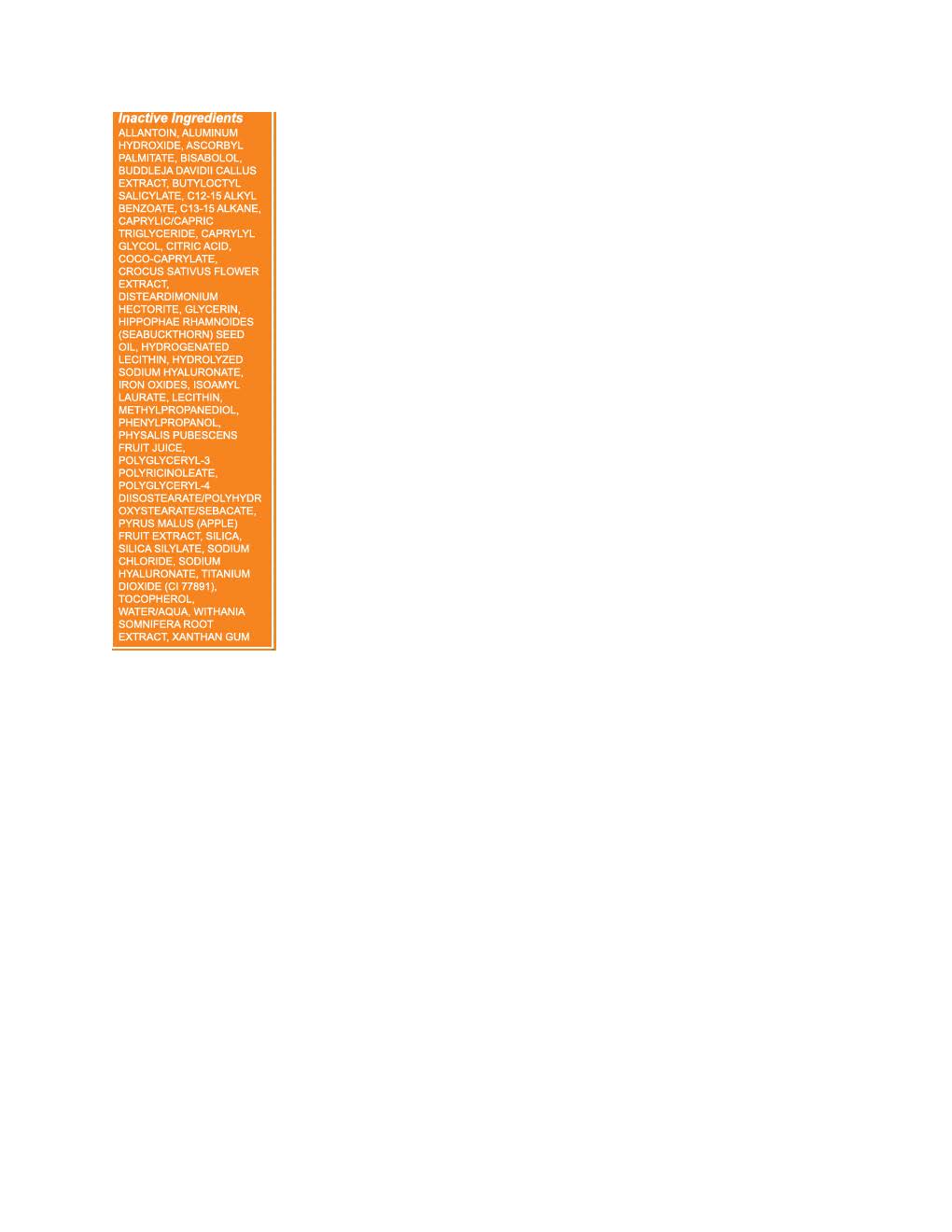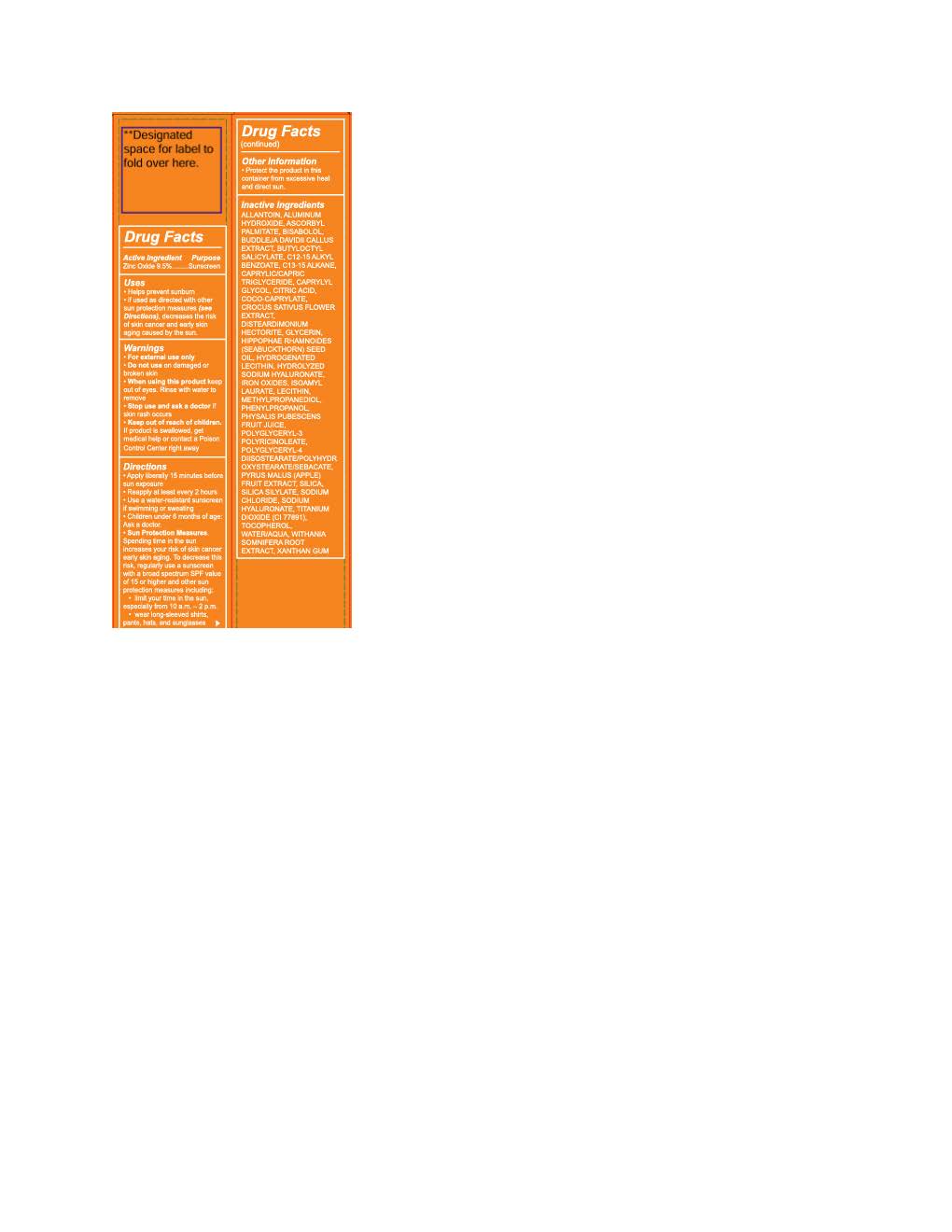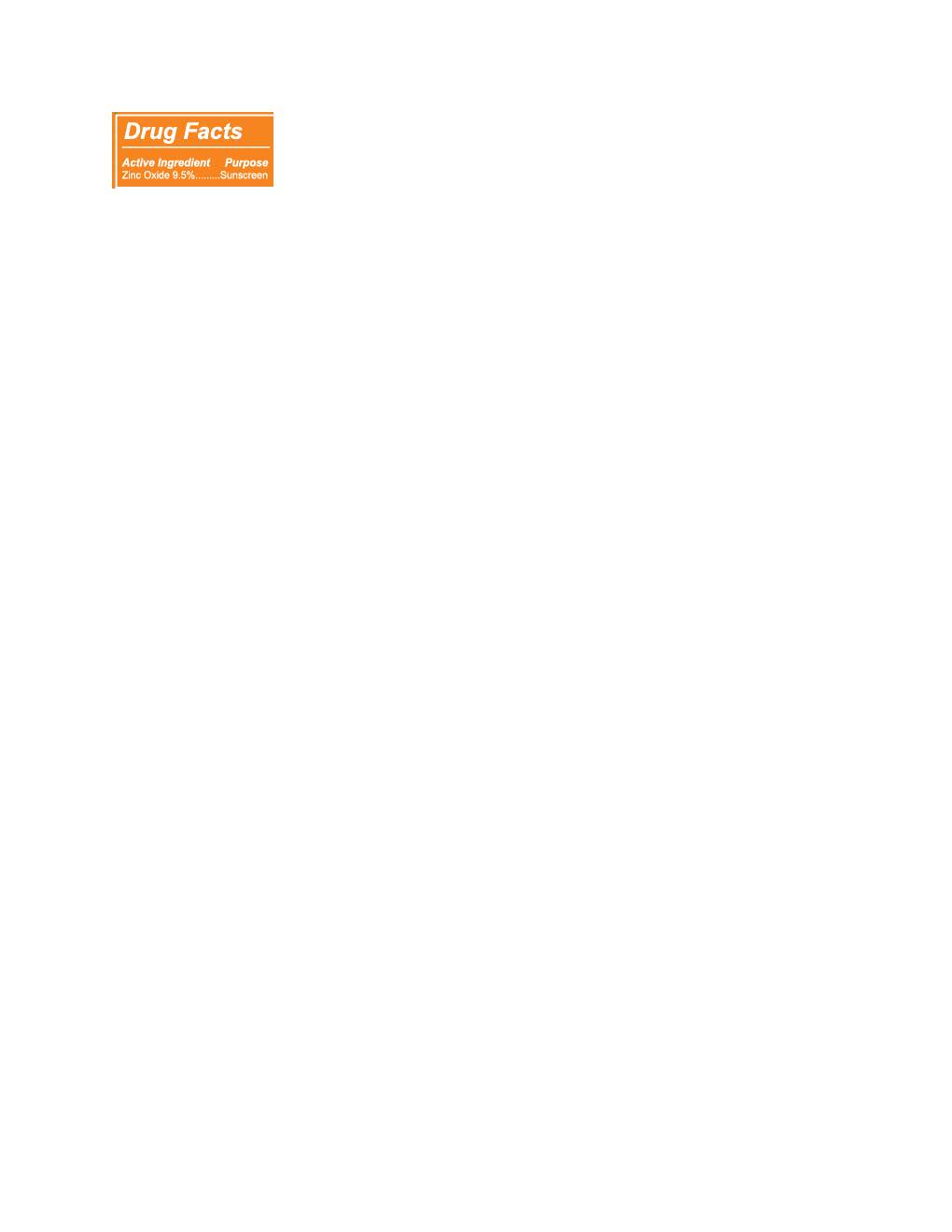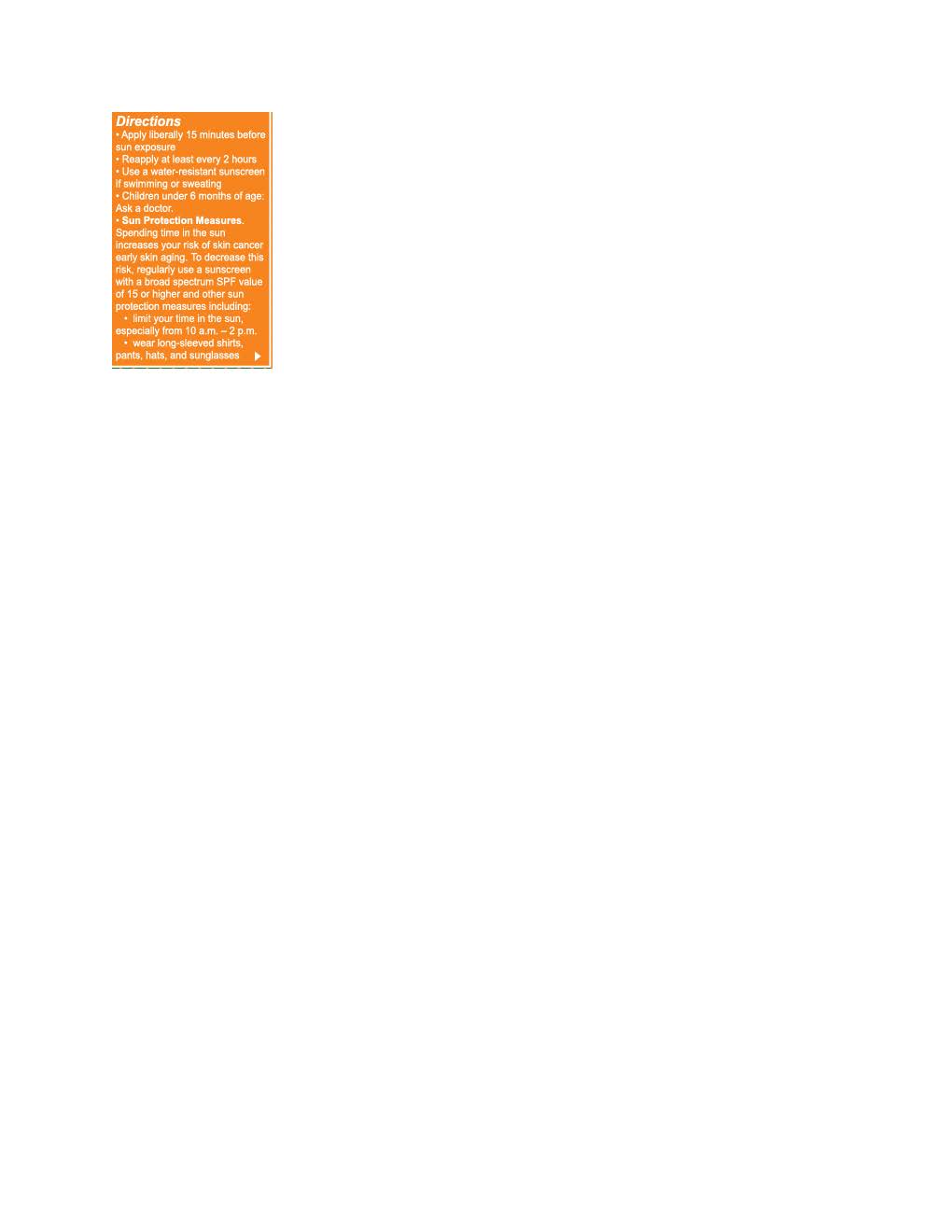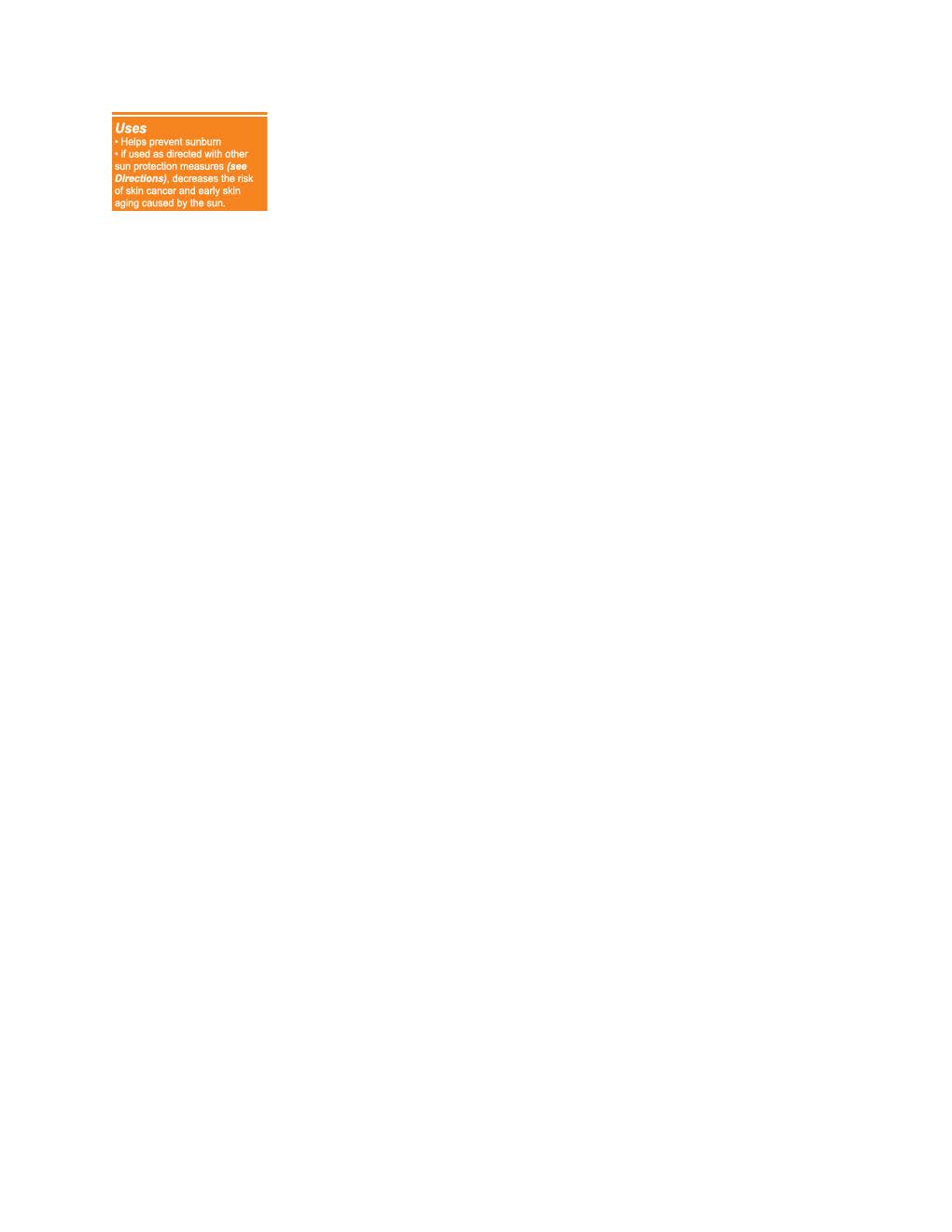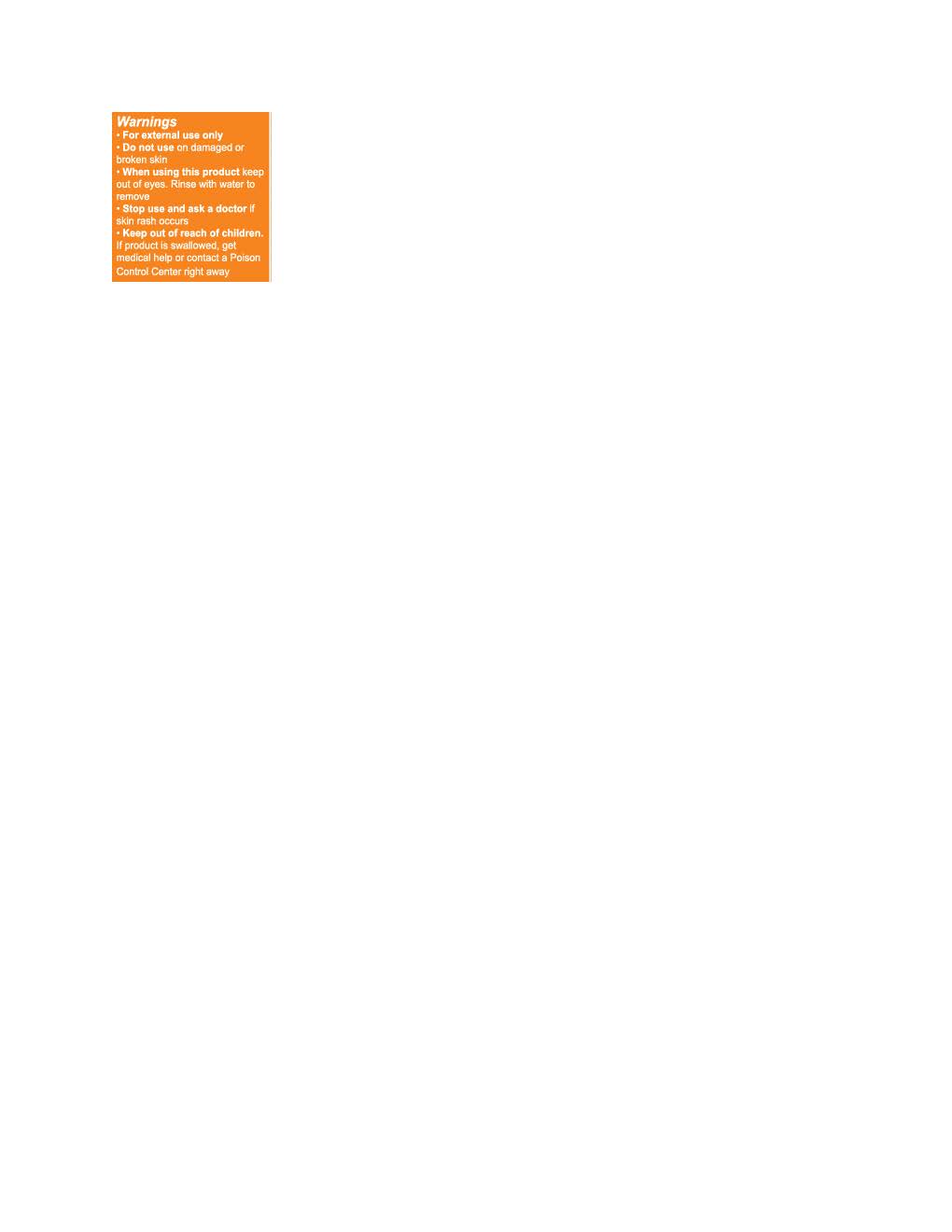 DRUG LABEL: Live Tinted Hueguard Skin Tint
NDC: 82153-192 | Form: LOTION
Manufacturer: Live Tinted
Category: otc | Type: HUMAN OTC DRUG LABEL
Date: 20251031

ACTIVE INGREDIENTS: ZINC OXIDE 132 mg/1 mL
INACTIVE INGREDIENTS: FERROUS OXIDE; TOCOPHEROL; SILICON DIOXIDE; CAPRYLYL GLYCOL; COCO-CAPRYLATE; LECITHIN, SOYBEAN; ALLANTOIN; ALKYL (C12-15) BENZOATE; .ALPHA.-BISABOLOL, (+)-; C13-15 ALKANE; BUTYLOCTYL SALICYLATE; ISOAMYL LAURATE; ASCORBYL PALMITATE; GLYCERIN; WATER; SODIUM CHLORIDE; POLYGLYCERYL-4 DIISOSTEARATE/POLYHYDROXYSTEARATE/SEBACATE; HIPPOPHAE RHAMNOIDES SEED OIL; DISTEARDIMONIUM HECTORITE; XANTHAN GUM; TITANIUM DIOXIDE; PHYSALIS PUBESCENS FRUIT JUICE; ALUMINUM HYDROXIDE; METHYLPROPANEDIOL

Live Tinted Huegaurd Skin Tint